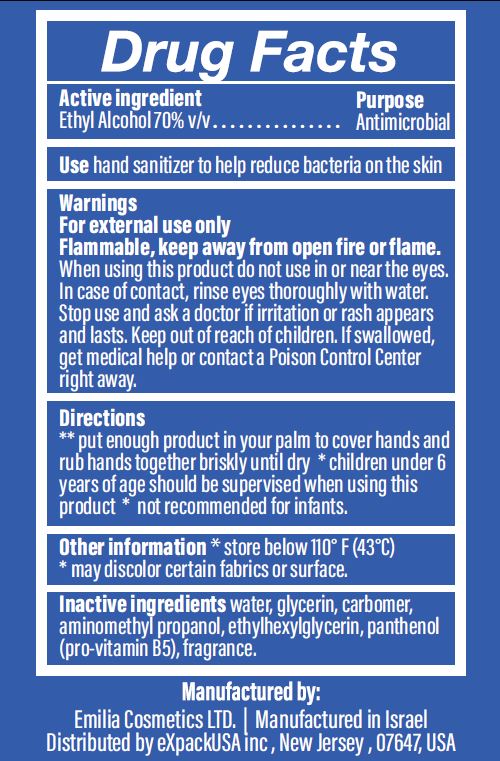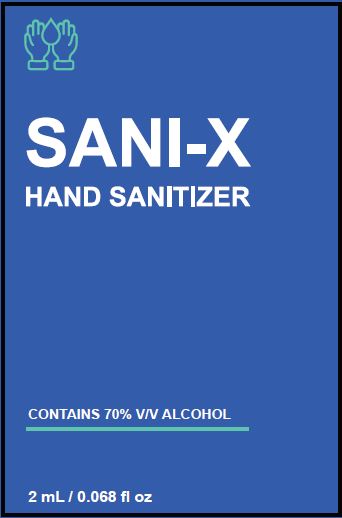 DRUG LABEL: HAND SANITIZER
NDC: 43219-104 | Form: GEL
Manufacturer: Emilia Cosmetics Ltd
Category: otc | Type: HUMAN OTC DRUG LABEL
Date: 20200523

ACTIVE INGREDIENTS: ALCOHOL 70 mL/100 mL
INACTIVE INGREDIENTS: WATER; GLYCERIN; CARBOMER HOMOPOLYMER, UNSPECIFIED TYPE; AMINOMETHYLPROPANOL; ETHYLHEXYLGLYCERIN; PANTHENOL

HAND SANITIZER

ACTIVE INGREDIENT

ETHYL ALCOHOL 70% V/V

PURPOSE

ANTIMICROBIAL

USES

HAND SANITIZER TO HELP REDUCE BACTERIA ON THE SKIN

WARNINGS

FOR EXTERNAL USE ONLY.

FLAMMABLE, KEEP AWAY FROM OPEN FIRE OR FLAME.

WHEN USING THIS PRODUCT DO NOT USE NEAR THE EYES. IN CASE OF CONTACT, RINSE EYES THOROUGHLY WITH WATER.

STOP USE AND ASK A DOCTOR IF IRRITATION OR RASH AND LASTS.

KEEP OUT OF REACH OF CHILDREN. IF SWALLOWED, GET MEDICAL HELP OR CONTACT A POISON CONTROL CENTER RIGHT AWAY.

DIRECTIONS

- PUT ENOUGH PRODUCT IN YOUR PALM TO COVER HANDS AND RUB HANDS BRISKLY TOGETHER UNTIL DRY.
- CHILDREN UNDER 6 YEARS OF AGE SHOULD BE SUPERVISED WHEN USING THIS PRODUCT.
- NOT RECOMMENDED FOR INFANTS.

OTHER INFORMATION

- STORE BELOW 110°F (43°C)
- MAY DISCOLOR CERTAIN FABRICS OR SURFACE.

INACTIVE INGREDIENTS

WATER, GLYCERIN, CARBOMER, AMINOMETHYL PROPANOL, ETHYLHEXYLGLYCERIN, PANTHENOL (PRO-VITAMIN B5), FRAGRANCE.